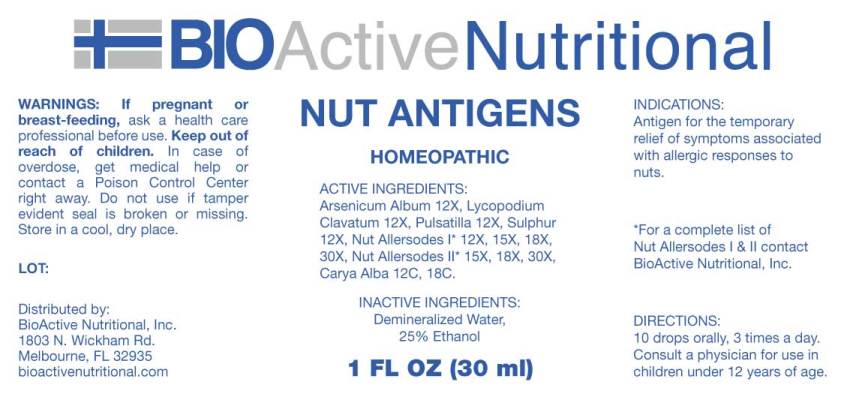 DRUG LABEL: Nut Antigens
NDC: 43857-0486 | Form: LIQUID
Manufacturer: BioActive Nutritional, Inc.
Category: homeopathic | Type: HUMAN OTC DRUG LABEL
Date: 20180710

ACTIVE INGREDIENTS: ARSENIC TRIOXIDE 12 [hp_X]/1 mL; LYCOPODIUM CLAVATUM SPORE 12 [hp_X]/1 mL; ANEMONE PRATENSIS 12 [hp_X]/1 mL; SULFUR 12 [hp_X]/1 mL; ALMOND 12 [hp_X]/1 mL; CASHEW 12 [hp_X]/1 mL; BLACK WALNUT 12 [hp_X]/1 mL; PECAN 12 [hp_X]/1 mL; COCONUT 12 [hp_X]/1 mL; OLIVE OIL 12 [hp_X]/1 mL; CHINESE CHESTNUT 12 [hp_X]/1 mL; TRAPA BICORNIS SEED 12 [hp_X]/1 mL; PINE NUT 12 [hp_X]/1 mL; MACADAMIA NUT 12 [hp_X]/1 mL; PISTACHIO 12 [hp_X]/1 mL; PEANUT 12 [hp_X]/1 mL; ENGLISH WALNUT 15 [hp_X]/1 mL; BRAZIL NUT 15 [hp_X]/1 mL; AMERICAN HAZELNUT 15 [hp_X]/1 mL; MOCKERNUT 12 [hp_C]/1 mL
INACTIVE INGREDIENTS: WATER; ALCOHOL

Drug Facts:

ACTIVE INGREDIENTS:

Arsenicum Album 12X, Lycopodium Clavatum 12X, Pulsatilla (Pratensis) 12X, Sulphur 12X, Almond (Nut) 12X, 15X, 18X, 30X, Cashew (Nut) 12X, 15X, 18X, 30X, Black Walnut (Nut) 12X, 15X, 18X, 30X, Pecan (Nut) 12X, 15X, 18X, 30X, Coconut 12X, 15X, 18X, 30X, Oleum Olea Europaea 12X, 15X, 18X, 30X, Chestnut (Nut) 12X, 15X, 18X, 30X, Water Chestnut (Nut) 12X, 15X, 18X, 30X, Pine Nut (Nut) 12X, 15X, 18X, 30X, Macadamia (Nut) 12X, 15X, 18X, 30X, Pistachio (Nut) 12X, 15X, 18X, 30X, Peanut (Nut) 15X, 18X, 30X, English Walnut (Nut) 15X, 18X, 30X, Brazil Nut (Nut) 15X, 18X, 30X, Hazelnut (Nut) 15X, 18X, 30X, Carya Alba 12C, 18C.

INDICATIONS:

Antigen for the temporary relief of symptoms associated with allergic responses to nuts.

WARNINGS:

If pregnant or breastfeeding, ask a health professional before use.

Keep out of reach of children. In case of overdose, get medical help or contact a Poison Control Center right away.

Do not use if tamper evident seal is broken or missing.

Store in a cool, dry place.

*For a complete list of Nut Allersodes I & II contact BioActive Nutritional, Inc.

Keep out of reach of children. In case of overdose, get medical help or contact a Poison Control Center right away.

DIRECTIONS:

10 drops orally, 3 times a day. Consult a physician for use in children under 12 years of age.

INDICATIONS:

Antigen for the temporary relief of symptoms associated with allergic responses to nuts.

INACTIVE INGREDIENTS:

Demineralized Water, 25% Ethanol.

QUESTIONS:

Distributed by:
BioActive Nutritional, Inc.
1803 N. Wickham Rd.
Melbourne, FL 32935
bioactivenutritional.com

PACKAGE LABEL DISPLAY:

BIOActive Nutritional

NUT ANTIGENS

HOMEOPATHIC

1 FL OZ (30 ml)